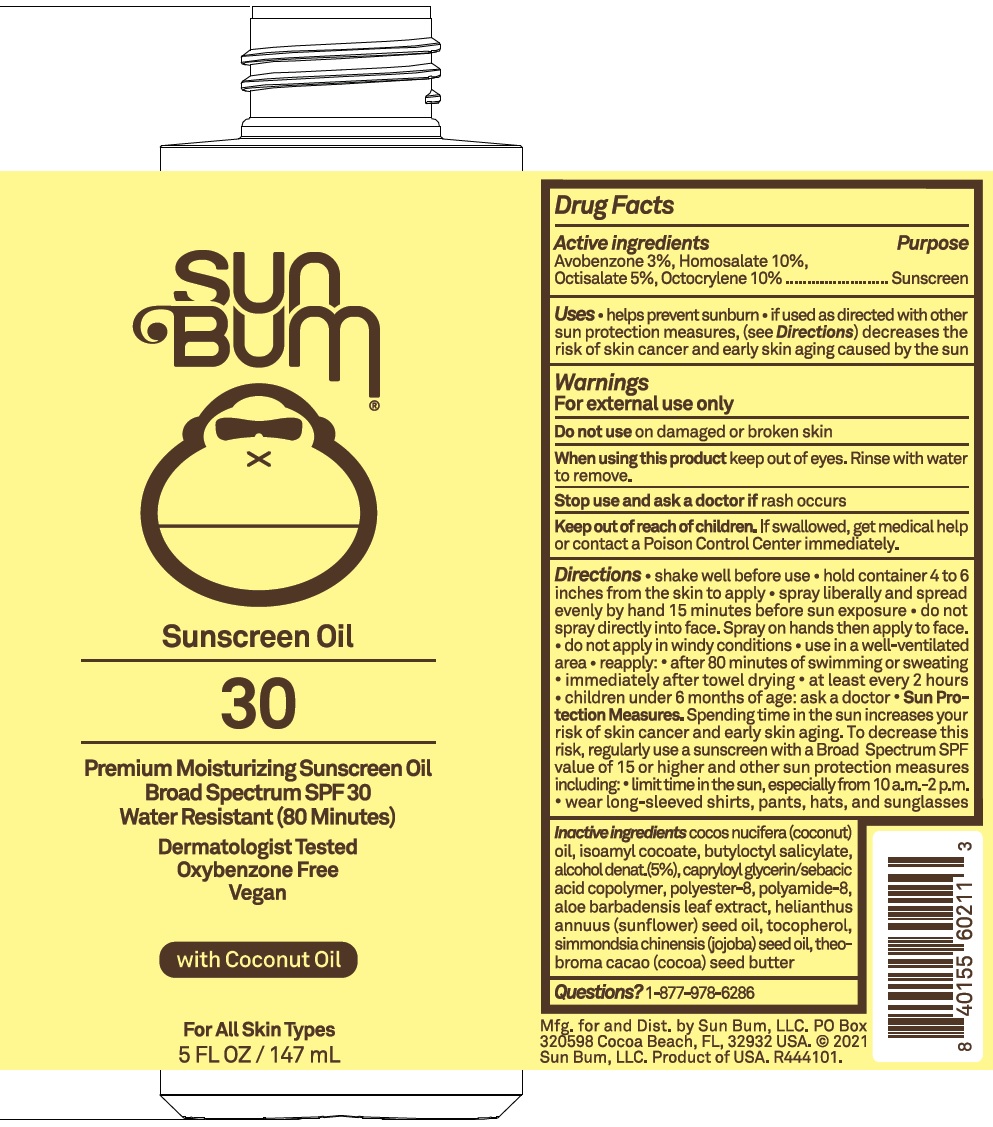 DRUG LABEL: Sun Bum Sunscreen Oil SPF 30 with Coconut Oil
NDC: 69039-644 | Form: OIL
Manufacturer: Sun Bum LLC
Category: otc | Type: HUMAN OTC DRUG LABEL
Date: 20220204

ACTIVE INGREDIENTS: AVOBENZONE 30 mg/1 mL; HOMOSALATE 100 mg/1 mL; OCTISALATE 50 mg/1 mL; OCTOCRYLENE 100 mg/1 mL
INACTIVE INGREDIENTS: POLYESTER-8 (1400 MW, CYANODIPHENYLPROPENOYL CAPPED); COCONUT OIL; ISOAMYL COCOATE; BUTYLOCTYL SALICYLATE; ALCOHOL; CAPRYLOYL GLYCERIN/SEBACIC ACID COPOLYMER (2000 MPA.S); POLYAMIDE-8 (4500 MW); ALOE VERA LEAF; SUNFLOWER OIL; TOCOPHEROL; JOJOBA OIL; COCOA BUTTER

Sun Bum Sunscreen Oil SPF 30 with Coconut Oil

Active ingredients

Avobenzone 3%, Homosalte 10%,
Octisalate 5%, Octocrylene 10%

Purpose

Sunscreen

Uses

- helps prevent sunburn
- if used as directed with other sun protection measures, (see Directions) decreases the risk of skin cancer and early skin aging caused by the sun

Warnings

For external use only

Do not use

on damaged or broken skin

When using this product

keep out of eyes. Rinse with water to remove.

Stop use and ask a doctor if

rash occurs

Keep out of reach of children.

If swallowed, get medical help or contact a Poison Control Center immediately.

Directions

• shake well before use • hold container 4 to 6 inches from the skin to apply • spray liberally and spread evenly by hand 15 minutes before sun exposure • do not spray directly into face. Spray on hands then apply to face. • do not apply in windy conditions • use in a well-ventilated area • reapply: • after 80 minutes of swimming or sweating • immediately after towel drying • at least every 2 hours • children under 6 months of age: ask a doctor • Sun Protection Measures. Spending time in the sun increases your risk of skin cancer and early skin aging. To decrease this risk, regularly use a sunscreen with a Broad Spectrum SPF value of 15 or higher and other sun protection measures including: • limit time in the sun, especially from 10 a.m.-2 p.m. • wear long-sleeved shirts, pants, hats and sunglasses

Inactive ingredients

cocos nucifera (coconut) oil, isoamyl cocoate, butyloctyl salicylate, alcohol denat.(5%) capryloyl glycerin/sebacic acid copolymer, polyster-8, polyamide-8, aloe barbadensis leaf extract, helianthus annuus (sunflower) seed oil, tocopherol, simmondsia chinenesis (jojoba) seed oil, theobroma cacao (cocoa) seed butter

Questions?

1-877-978-6286